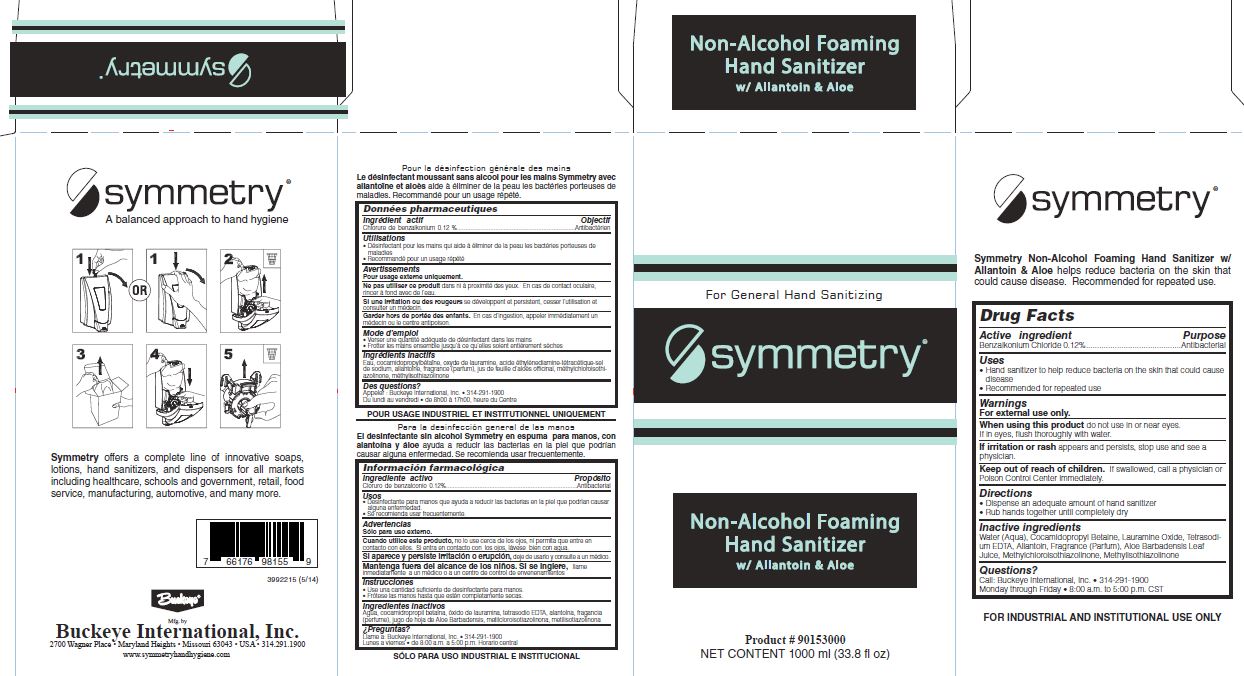 DRUG LABEL: Symmetry Non-Alcohol Foaming Hand Sanitizer  with Allantoin and Aloe
NDC: 30805-010 | Form: SOLUTION
Manufacturer: Buckeye International, Inc.
Category: otc | Type: HUMAN OTC DRUG LABEL
Date: 20241115

ACTIVE INGREDIENTS: BENZALKONIUM CHLORIDE 0.12 g/100 mL
INACTIVE INGREDIENTS: WATER; COCAMIDOPROPYL BETAINE; LAURAMINE OXIDE; EDETATE SODIUM; ALLANTOIN; ALOE VERA LEAF; METHYLCHLOROISOTHIAZOLINONE; METHYLISOTHIAZOLINONE

Drug Facts 30805-010

Active ingredient

Benzalkonium Chloride 0.12%

Purpose

Antibacterial

Uses

Hand sanitizer to help reduce bacteria on the skin that could cause disease

Recommended for repeated use

Warnings

For external use only.

When using this product do not use in or near eyes.

If in eyes, flush thoroughly with water.

ADVERSE REACTIONS

If irritation or rash appears and persists, stop use and see a physician.

Keep out of reach of children. If swallowed, call a physician or Poison Control Center immediately.

Directions

Dispense an adequate amount of hand sanitizer

Rub hands together until completely dry

Inactive ingredients

Water (Aqua), Cocamidopropyl Betaine, Lauramine Oxide, Tetrasodium EDTA, Allantoin, Fragrance (Parfum), Aloe Barbadensis Leaf Juice, Methylchloroisothiazolinone, Methylisothiazolinone

Questions?

Call: Buckeye International, Inc. 314-291-1900

Monday through Friday 8:00to 5:00 p.m. CST

PACKAGE LABEL

For General Hand Sanitizing

Symmetry

Non-Alcohol Foaming

Hand Sanitizer

w/ Allantoin and Aloe

Product # 90153000

Net Content 1000 ml (33.8 fl oz)